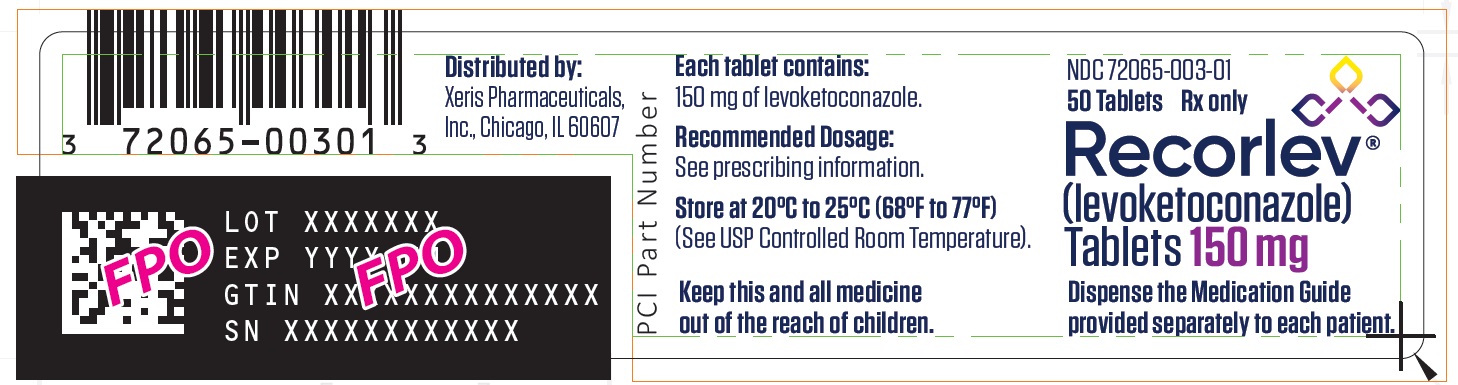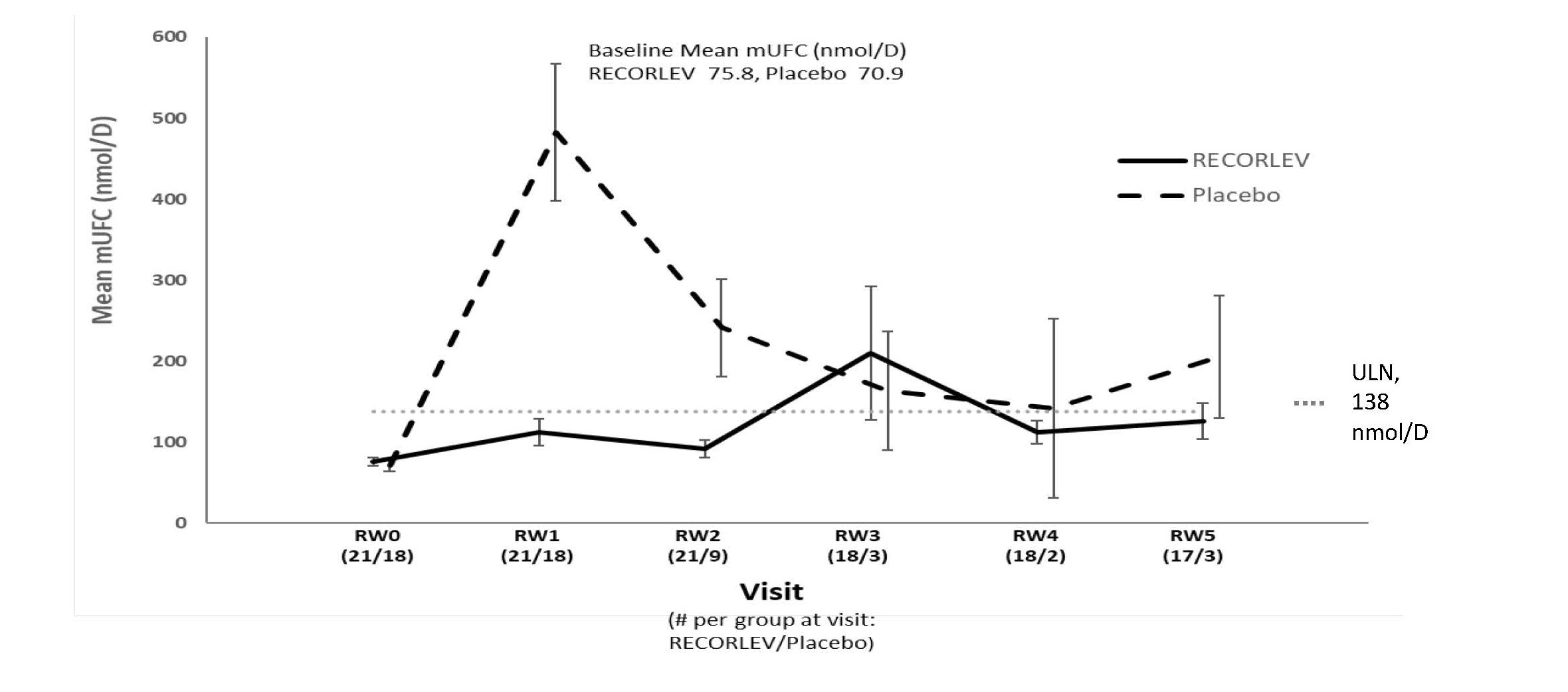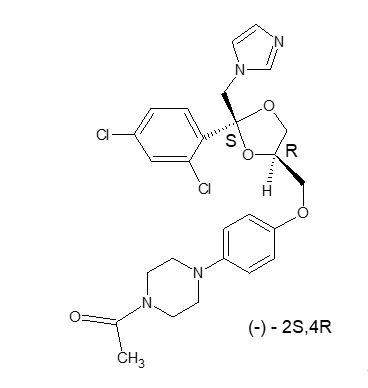 DRUG LABEL: Recorlev
NDC: 72065-003 | Form: TABLET
Manufacturer: Xeris Pharmaceuticals, Inc.
Category: prescription | Type: HUMAN PRESCRIPTION DRUG LABEL
Date: 20251223

ACTIVE INGREDIENTS: LEVOKETOCONAZOLE 150 mg/1 1

HIGHLIGHTS OF PRESCRIBING INFORMATION

These highlights do not include all the information needed to use RECORLEV safely and effectively. See full prescribing information for RECORLEV.
RECORLEV (levoketoconazole) tablets, oral
Initial U.S. Approval: 1981 (ketoconazole)

WARNING: HEPATOTOXICITY AND QT PROLONGATION

See full prescribing information for complete boxed warning.

- Cases of hepatotoxicity with fatal outcome or requiring liver transplantation have been reported with oral ketoconazole. Some patients had no obvious risk factors for liver disease. RECORLEV is associated with serious hepatotoxicity. Evaluate liver enzymes prior to and during treatment (5.1)
- RECORLEV is associated with dose-related QT interval prolongation. QT interval prolongation may result in life-threatening ventricular dysrhythmias such as torsades de pointes. Perform ECG prior to and during treatment (5.2)

1 INDICATIONS AND USAGE

RECORLEV is a cortisol synthesis inhibitor indicated for the treatment of endogenous hypercortisolemia in adult patients with Cushing’s syndrome for whom surgery is not an option or has not been curative (1)

Limitations of Use

RECORLEV is not approved for the treatment of fungal infections (1)

2 DOSAGE AND ADMINISTRATION

- Obtain baseline liver and electrocardiogram tests and correct hypokalemia and hypomagnesemia before starting RECORLEV (2.1)
- Initiate dosage at 150 mg orally twice daily, with or without food. Titrate dosage by 150 mg daily, no more frequently than every 2-3 weeks (2.2)
- Maximum recommended dosage is 1200 mg daily, administered as 600 mg twice daily (2.2)
- For additional recommendations on titration and monitoring for efficacy, see Full Prescribing Information (2.2)
- For recommendations on safety monitoring and dosage modifications for hepatotoxicity, QT prolongation and hypocortisolism, see Full Prescribing Information (2.3, 2.4)

3 DOSAGE FORMS AND STRENGTHS

Tablets: 150 mg (3)

4 CONTRAINDICATIONS

- Cirrhosis, acute liver disease or poorly controlled chronic liver disease, baseline AST or ALT > 3 times the upper limit of normal, recurrent symptomatic cholelithiasis, a prior history of drug induced liver injury due to ketoconazole or any azole antifungal therapy that required discontinuation of treatment, or extensive metastatic liver disease (4)
- Taking drugs that cause QT prolongation associated with ventricular arrhythmias, including torsades de pointes (4)
- Prolonged QTcF interval > 470 msec at baseline, history of torsades de pointes, ventricular tachycardia, ventricular fibrillation, or prolonged QT syndrome (4)
- Hypersensitivity to levoketoconazole, ketoconazole or any excipient in RECORLEV (4)
- Taking certain drugs that are sensitive substrates of CYP3A4 or CYP3A4 and P-gp (4)

5 WARNINGS AND PRECAUTIONS

- Hypocortisolism: Hypocortisolism has been reported with RECORLEV. Monitor patients for hypocortisolism. Dosage reduction or interruption may be necessary (5.3)
- Hypersensitivity Reactions:Hypersensitivity to RECORLEV has been reported. Anaphylaxis has been reported with oral ketoconazole (5.4)
- Risks Related to Decreased Testosterone: RECORLEV may lower serum testosterone in men and women. Inform patients to report associated symptoms (5.5)

6 ADVERSE REACTIONS

Most common adverse reactions (incidence > 20%) are nausea/vomiting, hypokalemia, hemorrhage/contusion, systemic hypertension, headache, hepatic injury, abnormal uterine bleeding, erythema, fatigue, abdominal pain/dyspepsia, arthritis, upper respiratory infection, myalgia, arrhythmia, back pain, insomnia/sleep disturbances, and peripheral edema. (6.1)

To report SUSPECTED ADVERSE REACTIONS, contact Xeris Pharmaceuticals, Inc. at 1-877-937-4737 or FDA at 1-800-FDA-1088 or www.fda.gov/medwatch.

7 DRUG INTERACTIONS

- Consult approved product labeling for drugs that are substrates of CYP3A4, P-gp, OCT2, and MATE prior to initiating RECORLEV (7.1)
- Sensitive CYP3A4 or CYP3A4 and P-gp Substrates: Concomitant use of RECORLEV with these substrates is contraindicated or not recommended (7.1)
- Atorvastatin: Use lowest atorvastatin dose possible and monitor for adverse reactions for dosages exceeding 20 mg daily (7.1)
- Metformin: Monitor glycemia, kidney function, and vitamin B12 and adjust metformin dosage as needed (7.1)
- Strong CYP3A4 Inhibitors or Inducers: Avoid use of these drugs 2 weeks before and during RECORLEV treatment (7.2)
- Gastric Acid Modulators: See Full Prescribing Information for recommendations regarding concomitant use with RECORLEV (7.2)

8 USE IN SPECIFIC POPULATIONS

Lactation: Advise not to breastfeed during treatment and for one day after final dose (8.2)

FULL PRESCRIBING INFORMATION

WARNING: HEPATOTOXICITY AND QT PROLONGATION

Hepatotoxicity

• Cases of hepatotoxicity with a fatal outcome or requiring liver transplantation have been reported with use of oral ketoconazole. Some patients had no obvious risk factors for liver disease. Serious hepatotoxicity has been reported in patients receiving RECORLEV [see Warnings and Precautions (5.1)].

• RECORLEV is contraindicated in patients with cirrhosis, acute liver disease or poorly controlled chronic liver disease, recurrent symptomatic cholelithiasis, a prior history of drug induced liver injury due to ketoconazole or any azole antifungal therapy that required discontinuation of treatment, or extensive metastatic liver disease [see Contraindications (4), Warnings and Precautions (5.1)].

• Evaluate liver enzymes prior to and during treatment. Interrupt RECORLEV treatment immediately if signs of hepatotoxicity occur [see Dosage and Administration (2.1, 2.3, 2.4), Warnings and Precautions (5.1)].

QT Prolongation
• RECORLEV is associated with dose-related QT interval prolongation. QT interval prolongation may lead to life-threatening ventricular dysrhythmias such as torsades de pointes [see Warnings and Precautions (5.2)].

• Coadministration of RECORLEV with other drugs that prolong the QT interval associated with ventricular arrhythmias, including torsades de pointes, and use in patients with a prolonged QTcF interval of greater than 470 msec at baseline, history of torsades de pointes, ventricular tachycardia, ventricular fibrillation, or long QT syndrome (including first-degree family history) are contraindicated [see Contraindications (4), Drug Interactions (7.1, 7.2)].

• Perform an ECG and correct hypokalemia and hypomagnesemia prior to and during treatment. Temporarily discontinue RECORLEV if QTcF interval exceeds 500 msec [Dosage and Administration (2.1, 2.3, 2.4)].

1 INDICATIONS AND USAGE

RECORLEV is indicated for the treatment of endogenous hypercortisolemia in adult patients with Cushing’s syndrome for whom surgery is not an option or has not been curative.

Limitations of Use

RECORLEV is not approved for the treatment of fungal infections. The safety and effectiveness of RECORLEV for the treatment of fungal infections have not been established.

2 DOSAGE AND ADMINISTRATION

2.1 Laboratory Testing Prior to RECORLEV Initiation

- Obtain baseline liver tests [alanine aminotransferase (ALT), aspartate aminotransferase (AST), total bilirubin]. Carefully consider the risks and potential benefits of initiating RECORLEV in patients with AST or ALT above normal but less than or equal to 3 times the upper limit of normal [see Contraindications (4), Warnings and Precautions (5.1)].
- Obtain baseline electrocardiogram (ECG) [see Contraindications (4), Warnings and Precautions (5.2)].
- Correct hypokalemia and hypomagnesemia prior to starting RECORLEV [see Warnings and Precautions (5.2)].

2.2 Recommended Dosage, Titration, and Monitoring for Efficacy

- Initiate dosage at 150 mg orally twice daily, with or without food [see Clinical Pharmacology (12.3)].
- Titrate the dosage by 150 mg daily, no more frequently than every 2-3 weeks based on 24-hour urine free cortisol levels and patient tolerability [see Dosage and Administration (2.4)] . Monitor cortisol levels from at least two 24-hour urine free cortisol collections every 2-3 weeks until an adequate clinical response is achieved.
- The maximum recommended dosage is 1200 mg per day, administered as 600 mg twice daily.
- The dosage may be reduced to 150 mg once daily if needed for reasons of tolerability [see Dosage and Administration (2.3, 2.4)].
- Once the maintenance dosage is achieved, monitor cortisol levels from at least two 24-hour urine free cortisol collections at least every 1-2 months or as indicated.
- If 24-hour urine free cortisol levels remain above the upper normal limit after treatment with the maximum recommended dosage of 1200 mg per day, or the patient cannot tolerate treatment with RECORLEV, consider discontinuing RECORLEV and switching patient to another therapy.

2.3 Monitoring for Safety

Perform the following monitoring during RECORLEV treatment. Refer to Dosage Interruptions and Modifications below for recommendations pertaining to management of liver, cortisol, or ECG abnormalities [see Dosage and Administration (2.4)].

Hepatotoxicity

- Serious hepatotoxicity has been reported in patients receiving RECORLEV, and therefore frequent monitoring of liver tests is recommended.
- Monitor liver enzymes and bilirubin weekly for at least 6 weeks after starting RECORLEV, every 2 weeks for the next 6 weeks, monthly for the next 3 months, and then as clinically indicated.
- After any dose interruption or dose increase, monitor on a weekly basis until a stable dosage is achieved [see Warnings and Precautions (5.1)].

QT Prolongation

- Conduct an ECG before each dose increase. After a stable dosage is established, monitor routinely for an effect on the QT interval.
- Monitor blood potassium and magnesium levels periodically during treatment [see Warnings and Precautions (5.2)].

Hypocortisolism

- Monitor 24-hour urine free cortisol, morning serum or plasma cortisol, and patient’s signs and symptoms for hypocortisolism periodically during RECORLEV treatment [see Warnings and Precautions (5.3)].

2.4 Dosage Interruptions and Modifications

Hepatotoxicity

Refer to Table 1 for management of hepatotoxicity [see Warnings and Precautions (5.1) ].

Table 1: Dosage Modification and Management for Hepatotoxicity
ALT or AST | Total Bilirubin | Recommendation
≥ 5 x ULN | Any value | Permanently discontinue RECORLEV.
≥ 3 x ULN | > 2 x ULN | Permanently discontinue RECORLEV.
≥ 3 to < 5 x ULN | ≤ 2 x ULN | - Temporarily discontinue RECORLEV. - Monitor liver tests every 3 days until the levels are stable, and then no less than every 7 to 10 days until tests have returned to baseline levels. - RECORLEV may be restarted at a lower dosage and titrated more slowly once liver tests normalize, and other possible contributing factors have been addressed. Before considering a dosage increase, monitor liver tests weekly for 1 month and then routinely thereafter. - Permanently discontinue RECORLEV if a liver test abnormality significantly above the patient’s baseline recurs after restarting RECORLEV.
> ULN to <3 x ULN | Any value | - If liver tests increase above the patient’s baseline, monitor liver tests no less than every 7 to 10 days until tests have returned to baseline levels. Consider temporary discontinuation of RECORLEV during this time. - If RECORLEV is discontinued, restart at a lower dosage and titrate more slowly once liver tests return to baseline and other possible contributing factors have been addressed. Before considering a dosage increase, monitor liver tests weekly for 1 month to ensure stability of liver tests.

QT Prolongation

- Temporarily discontinue RECORLEV if the QTcF interval is longer than 500 msec.
- After correction of other possible contributing factors (e.g., hypokalemia, hypomagnesemia, use of concomitant drugs), RECORLEV may be resumed at a lower dosage when the QTcF interval returns to 500 msec or less.
- If QT interval prolongation recurs after restarting RECORLEV, permanently discontinue RECORLEV [see Warnings and Precautions (5.2)] .

Hypocortisolism

- Decrease the dosage or temporarily discontinue RECORLEV if urine free cortisol or morning serum or plasma cortisol levels fall below the target range, there is a rapid decrease in cortisol levels, or if signs and/or symptoms consistent with hypocortisolism are reported.
- Stop RECORLEV and administer exogenous glucocorticoid replacement therapy if morning serum or plasma cortisol levels are below target range and signs and/or symptoms of adrenal insufficiency or hypocortisolism are present.
- Re-initiate RECORLEV at a lower dosage when cortisol levels are within target ranges and signs and/or symptoms of hypocortisolism have resolved [see Warnings and Precautions (5.3)] . The dosage may be titrated to the previous dose associated with hypocortisolism if the reduced dosage has been well tolerated and the reduced dosage does not achieve an adequate clinical response.

2.5 Missed Dose

If a dose of RECORLEV is missed, the patient should take the next dose at the regularly scheduled time.

3 DOSAGE FORMS AND STRENGTHS

Tablets: 150 mg, round, pink, film-coated, and imprinted in black ink with “LEV” above “150” on one side; the other side is plain.

4 CONTRAINDICATIONS

RECORLEV is contraindicated in patients:

- With cirrhosis, acute liver disease or poorly controlled chronic liver disease, baseline AST or ALT greater than 3 times the upper limit of normal, recurrent symptomatic cholelithiasis, a prior history of drug induced liver injury due to ketoconazole or any azole antifungal therapy that required discontinuation of treatment, or extensive metastatic liver disease [see Warnings and Precautions (5.1)] .
- Taking drugs that cause QT prolongation associated with ventricular arrhythmias, including torsades de pointes [see Warnings and Precautions (5.2)] .
- With a prolonged QTcF interval of greater than 470 msec at baseline, history of torsades de pointes, ventricular tachycardia, ventricular fibrillation, or long QT syndrome (including first-degree family history) [see Warnings and Precautions (5.2)] .
- With known hypersensitivity to levoketoconazole, ketoconazole or any excipient in RECORLEV [see Warnings and Precautions (5.4), Adverse Reactions (6.2)] .
- Taking certain drugs that are sensitive substrates of CYP3A4 or CYP3A4 and P-gP [see Drug Interactions (7.1)] .

5 WARNINGS AND PRECAUTIONS

5.1 Hepatotoxicity

Cases of hepatotoxicity with a fatal outcome or requiring liver transplantation have been reported with the use of oral ketoconazole, the racemic mixture from which levoketoconazole is derived. Some patients had no obvious risk factors for liver disease. Serious hepatotoxicity has been reported in patients receiving RECORLEV, irrespective of the dosages used or the treatment duration. Drug-induced liver injury (peak ALT or AST greater than 3 times upper limit of normal) occurred in 13% of patients using RECORLEV.

RECORLEV is contraindicated in patients with cirrhosis, acute liver disease or poorly controlled chronic liver disease, baseline AST or ALT greater than 3 times the upper limit of normal, recurrent symptomatic cholelithiasis, a prior history of drug induced liver injury due to ketoconazole or any azole antifungal therapy that required discontinuation of treatment, or extensive metastatic liver disease [see Contraindications (4)] .

Avoid concomitant use of RECORLEV with hepatotoxic drugs. Advise patient to avoid excessive alcohol consumption while on treatment with RECORLEV [see Drug Interactions (7.3)] .

Prompt recognition of liver injury is essential. At baseline, obtain liver tests [see Dosage and Administration (2.1)] . During RECORLEV treatment, regularly monitor liver enzymes, with more frequent monitoring during dosage titration [see Dosage and Administration (2.3)] .

Permanently discontinue RECORLEV treatment immediately if AST or ALT exceeds or is equal to 5 times the upper limit of normal, or AST or ALT exceeds or is equal to 3 times the upper limit of normal and total bilirubin concentration increases to more than 2 times the upper limit of normal.

Repeat liver tests within approximately 3 days following the initial abnormal liver test, until the levels are stable. Monitor at regular intervals thereafter, no less than every 7 to 10 days, until resolution of the abnormality (or return to baseline levels) or until an alternative cause has been identified [see Dosage and Administration (2.4)].

For AST or ALT elevations less than 3 times the upper limit of normal, or AST or ALT elevations equal to or greater than 3 to less than 5 times the upper limit of normal and total bilirubin concentration less than 2 times the upper limit of normal, monitor liver tests and manage hepatotoxicity with RECORLEV dosage interruption or modifications [see Dosage and Administration (2.4)] . If a liver abnormality significantly above the patient’s baseline recurs after restarting RECORLEV, permanently discontinue RECORLEV.

5.2 QT Prolongation

RECORLEV is associated with dose-related QT interval prolongation. QT interval prolongation may lead to life-threatening ventricular dysrhythmias such as torsades de pointes. During Studies 1 and 2, which excluded patients with baseline QTcF interval greater than 470 msec, 4 (2.4%) patients experienced QTcF>500 msec, and 23 (14.7%) patients experienced change-from-baseline QTcF >60 msec. Resolution typically occurred following a dosage interruption and in some cases correction of electrolyte abnormalities.

RECORLEV may also elevate plasma concentrations of certain drugs known to prolong QT intervals. Prolongation of the QT interval from certain drugs can result in life-threatening ventricular dysrhythmias such as torsades de pointes [see Drug Interactions (7.1, 7.2)] .

RECORLEV is contraindicated in patients taking other drugs known to cause QT interval prolongation associated with ventricular arrhythmias, including torsades de pointes, and is contraindicated in patients with a prolonged QTcF interval of greater than 470 msec at baseline, history of torsades de pointes, ventricular tachycardia, ventricular fibrillation, or long QT syndrome (including first-degree family history) [see Contraindications (4), Drug Interactions (7.1, 7.2)].

Use RECORLEV with caution in patients with other risk factors for QT prolongation, such as congestive heart failure, bradyarrhythmias, and uncorrected electrolyte abnormalities, with more frequent ECG monitoring considered.

Obtain a baseline QT interval measurement and regularly monitor ECG for an effect on the QT interval during RECORLEV treatment. Correct hypokalemia and/or hypomagnesemia prior to RECORLEV initiation and monitor periodically during treatment [see Dosage and Administration (2.1, 2.3)] . Temporarily discontinue RECORLEV if the QTcF interval exceeds 500 msec. After the QTcF interval returns to less than 500 msec and contributing factors are corrected, re-institution of RECORLEV at a lower dose may be considered. If QT interval prolongation recurs after restarting RECORLEV, permanently discontinue RECORLEV [see Dosage and Administration (2.4)] .

5.3 Hypocortisolism

RECORLEV lowers cortisol levels and may lead to hypocortisolism with a potential for life-threatening adrenal insufficiency. Adrenal insufficiency was observed in 7% of patients during the clinical program of RECORLEV [see Adverse Reactions (6.1)] . Lowering of cortisol levels can cause nausea, vomiting, fatigue, abdominal pain, loss of appetite, and dizziness. Significant lowering of serum cortisol levels may result in adrenal insufficiency that can be manifested by hypotension, abnormal electrolyte levels, and hypoglycemia.

Hypocortisolism may occur at any time during RECORLEV treatment. Evaluate patients for precipitating causes of hypocortisolism (infection, physical stress, etc.). Monitor 24-hour urine free cortisol, morning serum or plasma cortisol, and patient’s signs and symptoms periodically during RECORLEV treatment [see Dosage and Administration (2.3)] .

Decrease the dosage or temporarily discontinue RECORLEV if urine free cortisol or morning blood cortisol levels fall below the target range, there is a rapid decrease in cortisol levels, or if signs and/or symptoms consistent with hypocortisolism are reported [see Dosage and Administration (2.4)] .

Stop RECORLEV and administer exogenous glucocorticoid replacement therapy if morning serum or plasma cortisol levels are below target range and signs and/or symptoms of adrenal insufficiency, or hypocortisolism, are present. After RECORLEV discontinuation, cortisol suppression may persist beyond the 4- to 6- hour half-life of RECORLEV.

If treatment is interrupted due to hypocortisolism, re-initiate RECORLEV at a lower dosage when cortisol levels are within target ranges and patient’s signs and/or symptoms have resolved [see Dosage and Administration (2.4)] . The dosage may be titrated to the previous dose associated with hypocortisolism if the reduced dosage has been well tolerated and the reduced dosage does not achieve an adequate clinical response.

Educate patients on the symptoms associated with hypocortisolism and advise them to contact a healthcare provider if they occur.

5.4 Hypersensitivity Reactions

Hypersensitivity reactions have been reported in 1% of patients treated with RECORLEV in the clinical trials [see Adverse Reactions (6.1)] .

Anaphylaxis has been reported after a single dose of oral ketoconazole. Hypersensitivity reactions including urticaria have also been reported for ketoconazole [see Adverse Reactions (6.2)].

RECORLEV is contraindicated in patients with a known hypersensitivity to levoketoconazole, ketoconazole or any excipient in RECORLEV.

5.5 Risks Related to Decreased Testosterone

RECORLEV may lower serum testosterone in men and women. Potential clinical manifestations of decreased testosterone concentrations in men may include gynecomastia, impotence and oligospermia. Potential clinical manifestations of decreased testosterone concentrations in women include decreased libido and mood changes. Inform patients of the symptoms associated with low testosterone levels and advise patients to contact a healthcare provider if they occur.

6 ADVERSE REACTIONS

The following clinically significant adverse reactions are described elsewhere in the labeling:

- Hepatotoxicity [see Warnings and Precautions (5.1)]
- QT Prolongation [see Warnings and Precautions (5.2)]
- Hypocortisolism [see Warnings and Precautions (5.3)]
- Hypersensitivity Reactions [see Warnings and Precautions (5.4)]
- Risks related to Decreased Testosterone [see Warnings and Precautions (5.5)]

6.1 Clinical Trials Experience

Because clinical trials are conducted under widely varying conditions, adverse reaction rates observed in the clinical trials of a drug cannot be directly compared to rates in the clinical trials of another drug and may not reflect the rates observed in practice.

The safety of RECORLEV was evaluated in a multicenter, randomized-withdrawal study (Study 1) and in a multicenter, single-arm, open-label study (Study 2). During the two studies, 166 patients were exposed to RECORLEV, of which 104 patients were exposed for more than 6 months and 51 patients were exposed for at least 1 year. In both studies, most patients took RECORLEV twice daily in total daily dosages ranging from 300 mg to 1200 mg [see Clinical Studies (14)] .

Adverse reactions, excluding hepatic injury, reported in ≥10% of patients treated with RECORLEV in Study 1 are presented in Table 2listed in order of overall decreasing frequency of events.

Table 2: Adverse Reactions, Excluding Hepatic Injury, Occurring in ≥10% of Cushing’s Syndrome Patients Treated with RECORLEV in Study 1
Adverse Reaction Types | N= 84; n (%)
Nausea/Vomiting | 25 (30%)
Hypokalemia | 24 (29%)
Systemic hypertension | 20 (24%)
Hemorrhage/Contusiona | 19 (23%)
Headache | 18 (21%)
Abnormal uterine bleeding | 17 (20%)
Arrhythmiab | 16 (19%)
Fatigue | 15 (18%)
Upper respiratory infection | 15 (18%)
Abdominal pain/Dyspepsiac | 13 (15%)
Dizziness | 13 (15%)
Diarrhea | 13 (15%)
Decreased appetite | 11 (13%)
Dry mouth | 9 (11%)
Dry skin | 9 (11%)
Adrenal insufficiency | 8 (10%)
N = total number of patients, n = number of patients experiencing the event, (%) = proportion of patients experiencing the event.
aHemorrhage/contusion includes blood urine present, epistaxis, eye hemorrhage, gingival bleeding, hematoma, hematuria, hemorrhoidal hemorrhage, melena, and scleral hemorrhage.
bArrhythmia includes electrocardiogram QT prolonged, electrocardiogram T wave abnormal, palpitations, sinus tachycardia, tachycardia paroxysmal, and ventricular extrasystoles.
cAbdominal pain/dyspepsia includes abdominal pain, abdominal distension, dyspepsia, gastric disorder, and related terms

Other notable adverse reactions which occurred with a frequency less than 10% during Study 1 were: alopecia (6%), gastrointestinal infection (6%), urinary tract infection (6%), hypogonadism (2%), and hypersensitivity (1%).

Adverse reactions, excluding hepatic injury, reported in ≥10% of patients treated with RECORLEV in Study 2 are presented in Table 3listed in order of overall decreasing frequency of events.

Table 3: Adverse Reactions, Excluding Hepatic Injury, Occurring in ≥10% of Cushing’s Syndrome Patients Treated with RECORLEV in Study 2
Adverse Reaction Type | N = 94; n (%)
Erythemaa | 40 (43%)
Hemorrhage/Contusionb | 38 (40%)
Fatigue | 37 (39%)
Headache | 36 (38%)
Nausea/Vomiting | 35 (37%)
Abdominal pain/dyspepsiac | 31 (33%)
Arthritis | 26 (28%)
Upper respiratory infection | 26 (28%)
Myalgia | 24 (26%)
Abnormal uterine bleeding | 23 (24%)
Arrhythmiad | 23 (24%)
Back pain | 21 (22%)
Insomnia/Sleep disturbances | 21 (22%)
Peripheral edema | 19 (20%)
Systemic hypertension | 19 (20%)
Diarrhea | 18 (19%)
Pre-Syncope/Syncope | 17 (18%)
Rash | 16 (17%)
Urinary tract infection | 15 (16%)
Hypokalemia | 14 (15%)
Pruritus | 14 (15%)
Disturbance in attention | 13 (14%)
Irritability | 13 (14%)
Depression | 11 (12%)
Dry skin | 11 (12%)
Alopecia | 10 (11%)
N = total number of patients, n = number of patients experiencing the event, (%) = proportion of patients experiencing the event.
aErythema includes flushing.
bHemorrhage/Contusion includes blood urine present, conjunctival hemorrhage, ecchymosis, epistaxis, hematoma, hyphemia, and red blood cells urine.
cAbdominal pain/dyspepsia includes abdominal discomfort, abdominal distension, dyspepsia, gastritis, and other related terms.
dArrhythmia includes bradycardia, carotid pulse increased, defect conduction intraventricular, electrocardiogram QT prolonged, electrocardiogram T wave abnormal, heart rate increased, palpitations and sinus bradycardia.

Other notable adverse reactions which occurred with a frequency less than 10% during Study 2 were: gastrointestinal infections (5%), decreased libido (5%), hypogonadism (4%), adrenal insufficiency (3%), and gynecomastia (3%).

Description of Selected Adverse Reactions

Hepatic Injury and Elevated Liver Function Tests

Liver-related adverse reactions reported in patients treated with RECORLEV in Studies 1 and 2 are presented in Table 4. Table 5summarizes patients who had at least one ALT or AST measurement greater than the upper limit of reference range (ULN) in post baseline visits in Studies 1 and 2 combined who had tests in the normal range at baseline. There were 11 out of 166 patients who had an AST or ALT above the ULN to ˂3 x ULN at baseline. Of these patients, 3 had increases above 3 x ULN, and none had increases above 5 x ULN. Liver test abnormalities improved with cessation of medication.

Table 4: Hepatic Injury and Other Liver-Related Adverse Reactions Occurring in Cushing’s Syndrome Patients Treated with RECORLEV in Studies 1 and 2
 | N = 166; n (%)
At least one liver related adverse reaction | 45 (27%)
Liver enzyme elevationa | 33 (20%)
Drug-induced liver injury | 3 (2%)
Hepatic pain | 7 (4%)
Hepatic steatosis | 1 (1%)
Liver disorders | 4 (2%)
N = total number of patients, n = number of patients experiencing the event, (%) = proportion of patients experiencing the event.
aLiver enzyme elevation refers to elevation in aspartate aminotransferase, alanine aminotransferase, alkaline phosphatase, or gamma-glutamyl transferase.

Table 5: Elevations in AST or ALT post baseline in Cushing’s Syndrome Patients Treated with RECORLEV who had AST/ALT ≤ ULN at baseline in Studies 1 and 2
 | N = 155; n (%)a | Time to Event in Days; Median (Range)
AST or ALT > ULN | 70 (45%) | 73 (1-334)
AST or ALT >3 x ULN | 17 (11%) | 83 (26-232)
AST or ALT >5 x ULN | 7 (5%) | 104 (29-232)
AST or ALT >10 x ULN | 4 (3%) | 166 (36-252)
N = total number of patients, n = number of patients experiencing the event, (%) = proportion of patients experiencing the event.
aNot all elevations in liver enzymes were reported as adverse reactions during the studies.

QTc Interval Prolongation

In Study 1 and 2, there were 4 (2.4%) patients who experienced QTcF>500 msec, and 23 (14.7%) patients who experienced change-from-baseline QTcF >60 msec, respectively [see Warnings and Precautions (5.2)] . Adverse reactions reported around the same time that may have been associated with QT prolongation included fatigue, hypertension, nausea/vomiting, and ventricular extrasystoles (see Tables 2and 3).

Hypocortisolism

Hypocortisolism was reported in 11 (7%) of 166 patients across Studies 1 and 2, with events starting on median study day 96 (range 26-166). The majority of cases were managed by reducing the dosage or temporarily interrupting treatment with RECORLEV.

6.2 Postmarketing Experience

The following adverse reactions have been identified from published reports or postmarketing experience with ketoconazole. Because these reactions are reported voluntarily from a population of uncertain size, it is not always possible to reliably estimate their frequency or establish a causal relationship to ketoconazole exposure.

Blood and Lymphatic System Disorders: thrombocytopenia

Endocrine Disorders:adrenocortical insufficiency

Hepatobiliary Disorders:serious hepatotoxicity including hepatitis cholestatic, biopsy-confirmed hepatic necrosis, cirrhosis, hepatic failure including cases resulting in transplantation or death

Immune System Disorders:allergic conditions including anaphylactic shock, anaphylactic reaction, angioneurotic edema

Nervous System Disorders:reversible intracranial pressure increased (e.g., papilledema, fontanelle bulging in infants)

Reproductive System and Breast Disorders:erectile dysfunction; with dosages higher than 200 or 400mg daily, azoospermia.

Skin and Subcutaneous Tissue Disorders:acute generalized exanthematous pustulosis, photosensitivity

7 DRUG INTERACTIONS

7.1 Effect of RECORLEV on Other Drugs

Levoketoconazole is a strong CYP3A4 inhibitor, as well as an inhibitor of the drug transporters P-gp, OCT2, and MATE1 in vivo. In vitro, levoketoconazole inhibits CYP2B6 and CYP2C8. Concomitant use of RECORLEV with drugs that are substrates of these CYP enzymes and transporters may increase the risk of adverse reactions of these drugs.

Consult the approved product labeling for drugs that are substrates of CYP3A4, P-gp, OCT2, and MATE1 prior to initiating therapy with RECORLEV.

Table 6 presents drugs affected by RECORLEV that are contraindicated or not recommended for use during RECORLEV use. It also includes the clinical impact and management recommendations for concomitant use of RECORLEV with atorvastatin and metformin.

Table 6: Effect of RECORLEV on CYP3A4 and Transporter Substrates
CYP3A4 or CYP3A4 and P-gp SubstratesaThat May Prolong QT
Clinical Impact | Increases risk of QT prolongation and torsades de pointes.
Prevention or Management | Concomitant use of RECORLEV with other drugs that cause QT prolongation associated with ventricular arrhythmias, including torsades de pointes, is contraindicated [see Contraindications (4), Warnings and Precautions (5.2)].
Examples | Bosutinib, cisapride, clarithromycinb,cobimetinib, crizotinib, disopyramide, dofetilide, dronedarone, eliglustat (in patients that are poor or intermediate metabolizers of CYP2D6 and in patients taking strong or moderate CYP2D6 inhibitors), ivabradine, methadone, midostaurin, nicardipine, pimozide, quinidine, and ranolazine.
Sensitive CYP3A4 or CYP3A4 and P-gp Substratesa
Clinical Impact | Increases plasma concentrations of the substrate and may increase the risk of the substrate’s adverse reactions.
Prevention or Management | Concomitant use of RECORLEV with sensitive CYP3A4 or CYP3A4 and P-gp substrate drugs is contraindicated or not recommended [see Contraindications (4)] . Refer to the prescribing information of the substrate drug.
Examples | Alfentanil, avanafil, buspirone, conivaptanb, dabigatran etexilate, darifenacin, darunavir, digoxin, ebastine, everolimus, fexofenadine, ibrutinib, lomitapide, lovastatin, lurasidone, midazolam, naloxegol, nisoldipine, saquinavir, simvastatin, sirolimus, tacrolimus, tipranavirb, triazolam, and vardenafil.
CYP3A4 Substrate Atorvastatinc
Clinical Impact | Increases plasma concentration of atorvastatincand may increase the risk of atorvastatin-associated myopathy and rhabdomyolysis [see Clinical Pharmacology (12.3)] .
Prevention or Management | Concomitant use of RECORLEV with atorvastatin may require a dose reduction of atorvastatin. Use the lowest atorvastatin dose possible and monitor for adverse reactions when atorvastatin dosage exceeds 20 mg daily .
OCT2 and MATE Substrate Metforminc
Clinical Impact | Increases plasma concentration of metformincand may increase the risk of metformin’s adverse reactions [see Clinical Pharmacology (12.3)] . May increase plasma concentrations of other OCT2 and MATE substrates and increase the risk of their adverse reactions .
Prevention or Management | During RECORLEV dosage titration, monitor glycemia, kidney function, and Vitamin B12 in blood as per metformin prescribing information and adjust the dosage of metformin as needed.
aThe drugs listed are substrates for CYP3A4 and/or P-gp. Other metabolism and/or transporter pathways may also contribute to elimination of the substrate drug. Consult the approved product labeling for the substrate drug for more information.
bStrong CYP3A4 inhibitor [see Drug Interactions (7.2)] .
cBased on clinical drug interaction study with levoketoconazole.

7.2 Effect of Other Drugs on RECORLEV

Table 7 presents clinically significant drug interactions that affect RECORLEV.

Table 7: Clinically Significant Drug Interactions (Drugs that Affect RECORLEV)
Strong CYP3A4 Inhibitors
Clinical Impact | May increase plasma concentrations of levoketoconazole and increase the risk of adverse reactions from RECORLEV [see Clinical Pharmacology (12.3)] .
Prevention or Management | Administration of strong enzyme inhibitors of CYP3A4 with RECORLEV is not recommended. Avoid use of these drugs from 2 weeks before and during treatment with RECORLEV.
Examples | - Antivirals (e.g., ritonavir, ritonavir-boosted darunavir, ritonavir-boosted fosamprenavir, saquinavir) - Glucocorticoid and progesterone receptor antagonists (e.g., mifepristone)
Strong CYP3A4 Inducers
Clinical Impact | May decrease plasma concentrations of levoketoconazole and reduce the efficacy of RECORLEV
Prevention or Management | Administration of strong enzyme inducers of CYP3A4 with RECORLEV is not recommended. Avoid use of these drugs from 2 weeks before and during treatment with RECORLEV.
Examples | - Antibacterials (e.g., isoniazid, rifabutin, rifampicin) - Anticonvulsants (e.g., carbamazepine, phenytoin) - Antivirals (e.g., efavirenz, nevirapine) - Cytotoxic agents (e.g., mitotane)
Gastric Acid Neutralizers
Clinical Impact | Impairs absorption of levoketoconazole from RECORLEV.
Prevention or Management | Take gastric acid neutralizers a minimum of 2 hours after dosing with RECORLEV.
Examples | Aluminum hydroxide
Gastric Acid Suppressors
Clinical Impact | Impairs absorption of levoketoconazole from RECORLEV.
Prevention or Management | Avoid use of gastric acid suppressors with RECORLEV.
Examples | H2-receptor antagonists and proton pump inhibitors
Sucralfate
Clinical Impact | Impairs absorption of levoketoconazole from RECORLEV.
Prevention or Management | Avoid use of sucralfate with RECORLEV.

7.3 Alcohol

Patients should be advised against excessive alcohol consumption while using RECORLEV [see Warnings and Precautions (5.1)] . When used with alcohol cases of a disulfiram-like reaction have been reported with ketoconazole characterized by flushing, rash, peripheral edema, nausea, and headache. All symptoms completely resolved within a few hours.

8 USE IN SPECIFIC POPULATIONS

8.1 Pregnancy

Risk Summary

Levoketoconazole is the 2S, 4R enantiomer of ketoconazole. The available published data from case series and case-control studies on the use of the racemic ketoconazole during pregnancy are insufficient to determine a drug-associated risk of major birth defects. There are no available data on ketoconazole use during pregnancy to inform the risk of miscarriage. There are risks to the mother and fetus from untreated Cushing’s syndrome (see Clinical Considerations). No animal reproduction studies have been performed with levoketoconazole. However, levoketoconazole constituted about 70% of the exposure in humans and animals after racemic ketoconazole administration. In animal reproduction studies, embryotoxic effects were observed in pregnant mice, rats and rabbits, and fetal malformations were observed in rats, following oral dosing of racemic ketoconazole during the period of organogenesis at doses equal and less than the maximum recommended human dose (MRHD), respectively (see Data). Advise pregnant women of the potential risk to a fetus and consider whether the benefits of treatment with RECORLEV outweigh the risks.

The estimated background risk for major birth defects and miscarriage for the indicated population is unknown. All pregnancies have a background risk of birth defect, loss, or other adverse outcomes. In the U.S. general population, the estimated background risk of major birth defects and miscarriage in clinically recognized pregnancies is 2-4% and 15−20%, respectively.

Clinical Considerations

Disease-Associated Maternal and/or Embryo/Fetal Risk

Active Cushing’s syndrome during pregnancy has been associated with an increased risk of maternal and fetal morbidity and mortality (including gestational diabetes, gestational hypertension, pre-eclampsia, maternal death, miscarriage, intrauterine fetal demise, preterm birth and neonatal death).

Labor or Delivery

Dystocia (difficult labor) was noted in mice and rats administered oral ketoconazole during the period of organogenesis at exposures below the MRHD of levoketoconazole (by body surface area (BSA)). The clinical relevance of these findings for human is unknown.

Data

Animal Data

Racemic ketoconazole containing levoketoconazole was administered orally to rats, mice, and rabbits during the period of organogenesis. Levoketoconazole constituted about 70% of the exposure in animals after racemic ketoconazole administration.

Mice were administered 10, 20, and 40 mg/kg/day ketoconazole during the period of organogenesis (gestation days 6 to 18). Embryolethality (resorptions and still births) was observed at ≥ 20 mg/kg/day (below the MRHD of levoketoconazole based on BSA comparison). There was no maternal toxicity in mice up to the highest dose of 40 mg/kg/day (below the MRHD of levoketoconazole by BSA), however, females failed to deliver naturally and Cesarean examination 3 days after the due date showed increased resorptions and dead fetuses.

Rats were administered 10, 20, 40, and 80 mg/kg/day during the period of organogenesis (gestation days 6 to 18). Increased incidences of resorbed fetuses and still births were noted at ≥40 mg/kg/day (below the MRHD of levoketoconazole by BSA). Fetal malformations (oligodactyly, syndactyly, absence of metacarpal and/or metatarsal bones, and cleft palate) were noted at ≥80 mg/kg/day of ketoconazole (at the MRHD of levoketoconazole by BSA). Dystocia and prolonged gestation were observed in rats at ≥10 mg/kg/day (below the MRHD of levoketoconazole by BSA).

In rabbits, oral gavage doses of 0, 10 and 40 mg/kg/day ketoconazole were administered during the period of organogenesis (gestation days 6 through 18). Increased incidences of resorbed fetuses and still births were observed at ≥10 mg/kg/day (below MRHD of levoketoconazole by BSA).

8.2 Lactation

Risk Summary

Published data from one lactating woman show that ketoconazole is present in human milk in low amounts, with no reported adverse effects on the breastfed infant. However, these limited data are not sufficient to inform the risk to a breastfed infant with exposure to ketoconazole through breast milk. There are no data available on the effects of ketoconazole on milk production. Because of the potential for serious adverse reactions in the breastfed infant, including liver toxicity, advise patients not to breastfeed during treatment with RECORLEV and for one day (5 times the half-life) after the final dose.

8.3 Females and Males of Reproductive Potential

Infertility

RECORLEV may lower testosterone levels [see Warnings and Precautions (5.5)] and impair male and female fertility. Ketoconazole tablets (containing equal parts levoketoconazole and dextroketoconazole in a racemic mixture) have been demonstrated to lower serum testosterone in humans. Once therapy with ketoconazole tablets was discontinued, serum testosterone levels returned to baseline values. Testosterone levels are impaired with ketoconazole doses of 800 mg per day and abolished by 1600 mg per day. Clinical manifestations of decreased testosterone concentrations may include gynecomastia, impotence and oligospermia. In rat fertility studies, oral ketoconazole administered at doses equivalent to the MRHD of levoketoconazole by BSA during premating to implantation caused impaired fertility in male and female rats. In dog fertility studies, levoketoconazole targeted the reproductive tissues of male dogs in a dose-dependent manner with associated effects on spermatogenesis and maturation of spermatozoa. The effect was reversible upon discontinuation of treatment [see Nonclinical Toxicology (13.1)] .

8.4 Pediatric Use

The safety and effectiveness of RECORLEV in pediatric patients below the age of 18 have not been established.

8.5 Geriatric Use

Of the 166 patients in clinical trials with RECORLEV, 12 (7%) were 65 years and older, with one patient 75 years of age. Clinical studies of RECORLEV did not include sufficient number of patients 65 years of age and older to determine whether they respond differently from younger adult patients.

8.6 Renal Impairment

There is no experience with RECORLEV in patients with renal impairment. The overall pharmacokinetics of racemic ketoconazole in patients with renal impairment were not significantly different when compared with healthy subjects.

8.7 Hepatic Impairment

The use of RECORLEV is contraindicated in patients with cirrhosis, acute liver disease or poorly controlled chronic liver disease, recurrent symptomatic cholelithiasis, a prior history of drug induced liver injury due to ketoconazole or any azole antifungal therapy that required discontinuation of treatment, or extensive metastatic liver disease [see Contraindications (4), Warnings and Precautions (5.1)] .

10 OVERDOSAGE

In the event of acute accidental overdose, treatment consists of supportive and symptomatic measures. Within the first hour after ingestion, activated charcoal may be administered.

11 DESCRIPTION

RECORLEV (levoketoconazole) tablets contain levoketoconazole as the active ingredient. Levoketoconazole is the 2S,4R- enantiomer derived from racemic ketoconazole and is a cortisol synthesis inhibitor.

The chemical name of levoketoconazole is 2S,4R cis-1-acetyl-4-[4-[[2-(2,4-dichlorophenyl)-2-(1H-imidazol-1-ylmethyl)-1,3-dioxolan-4-yl] methoxyl]phenyl] piperazine.

The molecular formula of levoketoconazole is C26H28Cl2N4O4with a molecular mass of 531.43 g/mol.

Levoketoconazole is a white or almost white crystalline powder. It is very slightly soluble in water but soluble in aqueous solutions below pH 2.

RECORLEV tablets for oral administration contain 150 mg of levoketoconazole and the following inactive ingredients: colloidal silicon dioxide, lactose monohydrate, magnesium stearate, modified corn starch, and silicified microcrystalline cellulose. The non-functional pink film-coating contains iron oxide red, macrogol/polyethylene glycol 3350, polyvinyl alcohol partially hydrolyzed, talc, and titanium dioxide. The tablets are printed with a black imprinting ink that contains ammonium hydroxide 28%, ferrosoferric oxide, isopropyl alcohol, propylene glycol, and shellac glaze 45% (20% esterified) in ethanol.

12 CLINICAL PHARMACOLOGY

12.1 Mechanism of Action

In vitro, levoketoconazole inhibits key steps in the synthesis of cortisol and testosterone, principally those mediated by CYP11B1 (11β hydroxylase), CYP11A1 (the cholesterol side-chain cleavage enzyme, the first step in the conversion of cholesterol to pregnenolone), and CYP17A1 (17α-hydroxylase).

12.2 Pharmacodynamics

Cardiac Electrophysiology

The largest mean increase in QTc was 24 msec (UCI: 31 msec) following administration of levoketoconazole 150 mg to 600 mg twice daily (the approved recommended dosage) in patients with endogenous Cushing’s syndrome. The increase in QTc was dose-related.

12.3 Pharmacokinetics

Absorption

Peak plasma concentrations of levoketoconazole occur approximately 1.5 to 2 hours following oral administration of a single dose of RECORLEV under fasted conditions regardless of dose. In healthy volunteers, Cmaxincreases approximately proportionally with dose, while AUC increases greater than dose proportionally from 150 mg to 600 mg. Levoketoconazole accumulates in plasma during multiple dosing of RECORLEV.

Levoketoconazole is a substrate of the intestinal (and liver) efflux transporter, P-gp.

Effect of Food

In a healthy volunteer study (N = 24), subjects administered a single, 600 mg oral dose of RECORLEV tablets with a high-fat meal (total caloric content of 875 calories; 160 protein calories, 170 carbohydrate calories, and 545 fat calories) resulted in an increase of AUC by 30% and no change in Cmax. The median Tmaxwas delayed from 2 to 4 hours. These changes are not considered to be clinically significant.

Distribution

Levoketoconazole has an apparent volume of distribution of 31 to 41 L, approximating total body water. Protein binding of levoketoconazole in human plasma is high (99.3%).

Elimination

Metabolism

No in vitro or in vivo studies of levoketoconazole metabolism have been performed. Racemic ketoconazole is metabolized extensively in the liver to several inactive metabolites (with respect to antifungal activity). CYP3A4 is the major enzyme involved in the metabolism of ketoconazole. The major identified metabolic pathways are oxidation and degradation of the imidazole and piperazine rings. In addition, oxidative O-dealkylation and aromatic hydroxylation occurs.

Excretion

Levoketoconazole is eliminated from plasma with a half-life of 3 to 4.5 hours after a single dose and 4 to 6 hours after multiple doses.

A mass-balance study has not been performed with levoketoconazole. Approximately 13% of a racemic ketoconazole dose is excreted in the urine, of which 2 to 4% is unchanged drug. The major route of excretion is through the bile into the intestinal tract with about 57% being excreted in the feces.

Specific Populations

Population pharmacokinetic modeling data from patients with Cushing’s syndrome suggest there is no impact of age or sex on the pharmacokinetics of levoketoconazole. The pharmacokinetics of levoketoconazole have not been formally studied in geriatric patients. Levoketoconazole has not been studied in patients younger than 18 years of age. Differences in pharmacokinetics among race/ethnicity groups are unknown.

Patients with Renal or Hepatic Impairment

Levoketoconazole has not been studied in patients with renal or hepatic impairment. The overall pharmacokinetics of racemic ketoconazole was not significantly altered in patients with renal failure when compared with healthy volunteers. [see Contraindications (4)]. Given the extensive hepatic metabolism of ketoconazole, it is expected that clearance would be reduced in patients with impaired liver function.

Drug Interaction Studies

Levoketoconazole is a strong CYP3A4 inhibitor, as well as an inhibitor of the drug transporters P-gp, OCT2, and MATE1 in vivo. Concomitant administration of medications that are substrates of these enzymes or transporters may have their plasma concentrations affected by RECORLEV [see Drug Interactions (7.1)] .

Clinical drug interaction studies were conducted to evaluate the effects of levoketoconazole on the pharmacokinetics of atorvastatin, felodipine, and metformin in healthy volunteers. Results are displayed in Table 8. For clinical recommendations regarding these interactions, [see Drug Interactions (7.1)] .

Table 8: Change in Pharmacokinetic Parameters for Coadministered Drug in the Presence of Levoketoconazole
Coadministered Drug | N | Levoketoconazole Dose | Ratio of Least Square Means (90% Confidence Interval)a
Coadministered Drug | N | Levoketoconazole Dose | AUC0-∞ | Cmax
Atorvastatin | 23 | 400 mg once daily | 317.6%; (286.6-352.0%) | 96.7%; (82.3 – 113.6%)
Felodipine | 14 | 400 mg once daily | 1007.3%; (868.8-1167.9%) | 937.1%; (757.9-1158.8%)
Metformin | 17 | 450 mg twicedaily | 220%; (203 – 239%) | 182%; (168 – 197%)
aFor coadministered drug + levoketoconazole vs coadministered drug alone.

In Vitro Studies Where Drug Interaction Potential was not Further Evaluated Clinically

In vitro, levoketoconazole inhibits CYP2B6 and CYP2C8, and induces CYP1A2.

Levoketoconazole does not inhibit CYP1A2, CYP2C9, CYP2C19, or CYP2D6, does not induce CYP2B6, and does not inhibit the OATP1B3, OAT1, OAT3, or MATE2-K transporters.

13 NONCLINICAL TOXICOLOGY

13.1 Carcinogenesis, Mutagenesis, Impairment of Fertility

Carcinogenesis

Levoketoconazole has not been evaluated for carcinogenic effects. Ketoconazole was not carcinogenic in an 18-month, oral study in Swiss albino mice or a 24-month oral carcinogenicity study in Wistar rats at dose levels of 5, 20 and 80 mg/kg/day of ketoconazole. The high dose in these studies was less than the MRHD of levoketoconazole in the mouse and equal to the MRHD of levoketoconazole in rats based on a BSA comparison.

Mutagenesis

Mutagenic potential of levoketoconazole has not been evaluated. Ketoconazole did not show any signs of mutagenic potential when evaluated using the dominant lethal mutation test or the Ames Salmonella microsomal activator assay.

Impairment of Fertility

In animal fertility studies, oral ketoconazole impaired both male and female fertility in rats in a dose and duration dependent manner. In female rats, oral doses up to 40 mg/kg of ketoconazole (lower than the MRHD for levoketoconazole by BSA) had no effect on fertility. Doses of ≥75 mg/kg of ketoconazole (at the MRHD for levoketoconazole by BSA) decreased the pregnancy rate and number of implantation sites, and in males decreased sperm content (motility, count, morphology), which correlated with lower plasma testosterone levels and testicular histological changes. When administered for longer durations (up to 3 months), decreased fertility in male rats was observed at doses as low as 24 mg/kg/day of ketoconazole (lower than the MRHD for levoketoconazole by BSA).

In male beagle dogs, an oral dose of 25 mg/kg/day ketoconazole for up to 4 weeks (at the MRHD for levoketoconazole by BSA) resulted in decreased sperm motility, decreased sperm count, increased abnormal sperm and atrophy of the testes. These effects were reversed after withdrawal of treatment.

14 CLINICAL STUDIES

The effectiveness of RECORLEV in patients with Cushing's syndrome was evaluated in two studies, Study 1 and Study 2.

Study 1

Study 1 consisted of an open-label dose titration and maintenance phase of up to 19 weeks duration, followed by an 8-week double-blind, placebo-controlled, randomized withdrawal phase (NCT03277690).

Study 1 enrolled 84 Cushing’s syndrome patients with persistent or recurrent disease despite surgery, previously medically treated patients, and previously untreated patients. The etiology of Cushing's syndrome was Cushing's disease for 70 (83%) patients, adrenal Cushing’s syndrome in 8 (10%) patients, ectopic ACTH secretion for 2 (2%) patients, and unknown for 4 (5%) patients. Patients with pituitary or adrenal carcinoma were excluded. Twelve (14%) patients who had previously received RECORLEV in Study 2 were also enrolled in Study 1. The mean age at baseline was 45 years; 76% of patients were female. Overall, the mean time since diagnosis was 63 months before treatment with the first dose in this study. Persistence or recurrence of Cushing’s syndrome was evidenced by the mean of three 24-hour UFC levels greater than or equal to 1.5 × upper limit of normal (normal range: 11 to 138 nmol/day or 4 to 50 µg/day). For the 79 patients who underwent dose titration, the mean mUFC (SD) at study baseline was 785 nmol/day (932), which corresponds to approximately 6 × ULN. The median mUFC at baseline was 479 nmol/day, which corresponds to approximately 3.5 × ULN. Seventy-two (72) patients were naïve to treatment with RECORLEV, seven (7) patients were treated with RECORLEV in Study 2 but were not on therapeutic dose (dose at which mUFC level was ≤ ULN, or maximum allowed dose [600 mg twice daily] had been reached, or a clinically meaningful partial response based on clinical judgement, and the maximum tolerated dose had been reached) prior to the enrollment in Study 1. Five (5) of 84 patients continued treatment with therapeutic dose of RECORLEV prior to the enrollment in Study 1; these patients were enrolled directly in the randomized withdrawal phase.

Dose Titration and Maintenance Phase (14-19 weeks)

Seventy-nine (79) patients entered the dose titration and maintenance phase. Patients naïve to treatment with RECORLEV were started on 150 mg of RECORLEV orally twice daily. Patients who previously participated in Study 2 could start on a dose higher than 150 mg twice daily. The dose could be titrated in 150-mg increments at 2-week intervals to a maximum of 600 mg twice daily to achieve mUFC within the normal range. The dose was increased if mUFC was above ULN and was reduced based on individual tolerability. Patients who achieved a stable therapeutic dose for at least 4 weeks and achieved a normal mUFC at the end of the dose titration and maintenance phase were eligible for the randomized withdrawal phase.

Randomized Withdrawal Phase (approximately 8 weeks)

Forty-four (44) patients entered the randomized withdrawal phase: 39 patients from dose titration and maintenance phase and 5 patients directly from Study 2. Patients were randomized in a 1:1 ratio to either continue RECORLEV or receive matched placebo for approximately 2 months or until early rescue was necessary (i.e., for mUFC >1.5 × ULN).

Efficacy Assessment and Results

The key secondary efficacy endpoint was the proportion of patients with mUFC normalization, defined as a patient with mUFC at or below the ULN at the end of randomized withdrawal phase without meeting a requirement for early rescue during the randomized withdrawal phase.

Out of the 79 patients who entered the dose titration and maintenance phase, 37 (47%) patients who met the requirement to be on a stable therapeutic dose for at least 4 weeks and established normal mUFC at the end of the dose titration and maintenance phase, and 2 patients who did not meet the requirement due to abnormal mUFC, continued to the randomized-withdrawal phase. Out of 5 patients from Study 2 who were enrolled directly in the randomized withdrawal phase, 2 patients had normal mUFC.

Among the 39 patients who had normal mUFC at the randomized withdrawal phase baseline, 21 were randomized to the RECORLEV group and 18 to the placebo group. The number and percent of patients who had normal mUFC at the end of the randomized withdrawal phase was 11/21 (52.4%) in RECORLEV group and 1/18 (5.6%) in placebo group, and the treatment difference (CI) was 46.8% (16.5%, 70.2%). Out of 11 patients with normal mUFC at the end of the randomized-withdrawal phase, 7 patients in the RECORLEV group had normal mUFC throughout the randomized-withdrawal phase. Figure 1 depicts the mUFC during the randomized-withdrawal phase of Study 1. The line for the placebo group should be interpreted with caution as majority of placebo patients were rescued early due to high mUFC levels and were not included in the analysis.

Figure 1: Line Plot of the Mean Urinary Free Cortisol During the Randomized Withdrawal Phase of Study 1 - Observed Mean (± SE)

mUFC = Mean Urinary Free Cortisol; RW = Randomized Withdrawal; SE = Standard Error; ULN = Upper Limit of Normal

Only patients who remained in study with non-missing mUFC are included in the analysis

Study 2

Supportive evidence of efficacy was obtained from Study 2 which was a multicenter, single-arm, open-label study that consisted of three study phases (dose titration, maintenance, and extended evaluation) for a total estimated treatment duration of up to 73 weeks (NCT01838551)

Study 2 enrolled 94 Cushing’s syndrome patients naïve to the treatment with RECORLEV with persistent or recurrent disease despite surgery, previously medically treated patients, and previously untreated patients. The etiology of Cushing's syndrome was benign pituitary adenoma for 80 (85%) patients, adrenal Cushing’s syndrome in 8 (9%) patients, ectopic ACTH secretion for 1 (1%) patient, and unknown source for 5 (5%) patients. Patients with pituitary or adrenal carcinoma were excluded. The mean age at enrollment was 44 years; 82% of patients were female. Overall, the mean time since diagnosis was 68 months before treatment with the first dose in this study. Persistence or recurrence of Cushing’s syndrome was evidenced by the mean of four 24-hour UFC (mUFC) levels greater than or equal to 1.5 times upper limit of normal (ULN); normal range: 11 to 138 nmol/day or 4 to 50 µg/day). The mean (SD) of the mean urinary free cortisol (mUFC) at baseline was 243 µg/day (269), which corresponds to approximately 5 x ULN. The median mUFC at baseline was 148 µg/day (range 59-1510), which corresponds to approximately 3 x ULN.

Dose Titration Phase (2 to 21 weeks)

Ninety-four (94) patients received a starting dosage of 150 mg RECORLEV orally twice daily that was titrated approximately every 2 to 3 weeks if mUFC was above the ULN to a maximum of 600 mg twice daily. Patients who achieved a therapeutic dose were continued to the maintenance phase. Therapeutic dose was defined as a dose at which mUFC level was ≤ ULN, or maximum allowed dose (600 mg twice daily) had been reached, or a clinically meaningful partial response based on clinical judgement, and the maximum tolerated dose had been reached.

Maintenance Phase (6 months)

Seventy-seven (77) patients who achieved a therapeutic dose in the dose titration phase entered the maintenance phase and continued treatment with therapeutic dose of RECORLEV for 6 months. The dose of RECORLEV was allowed to be decreased for safety or tolerability reasons or increased for loss of efficacy. The primary efficacy endpoint was evaluated at the end of maintenance phase.

Extended Evaluation Phase (6 months)

Sixty (60) patients entered the extended evaluation phase in which treatment with RECORLEV continued for an additional 6 months.

Efficacy Assessment and Results

The primary efficacy endpoint of the study was the proportion of patients with normalization of mUFC at the end of the 6-month maintenance phase. Normalization of mUFC was defined as mUFC at or below the ULN based on central laboratory result without requiring a dose increase during the maintenance phase. At the end of the maintenance phase, 29 of 94 patients (30.9%, 95% exact confidence interval 21.7%, 41.2%) met the primary endpoint.

Out of the 94 patients who enrolled in Study 2, 63 (67%) patients had normal mUFC at the end of the titration phase, 29 (30.9%) patients had normal mUFC at the end of the maintenance phase without any dose increase during the maintenance phase, and 16 (17%) patients had normal mUFC at the end of the extended evaluation phase without dose increase during maintenance or extended evaluation phase. However, because 51% of patients discontinued treatment prematurely due to adverse reaction, lack of efficacy, or other reasons, these results should be interpreted with caution.

16 HOW SUPPLIED/STORAGE AND HANDLING

How Supplied

RECORLEV (levoketoconazole) tablets, 150 mg are round, biconvex tablets, with a pink-colored film coating, containing 150 mg of levoketoconazole, and imprinted with an identification code in black ink with the “LEV” printed above the “150” on one side. The other side is plain.

Bottles of 50 with child-resistant closure: NDC 72065-003-01

Storage

Store RECORLEV at 20° to 25°C (68° to 77°F); excursions permitted between 15° to 30°C (59° to 86°F) (see USP controlled room temperature).

17 PATIENT COUNSELING INFORMATION

Advise the patient to read the FDA-approved patient labeling (Patient Information).

Monitoring

Instruct patients on the importance of laboratory monitoring and adherence to their return-visit schedule [see Dosage and Administration (2.3, 2.4)] .

Liver Injury

Inform patients that RECORLEV may cause liver injury. Advise patients of the signs and symptoms of hepatotoxicity (e.g., right upper quadrant pain associated with nausea, unusual fatigue, signs of jaundice, unusual bruising or bleeding). Advise patients to contact their healthcare provider immediately for signs or symptoms of hepatotoxicity. Advise patients that liver tests will be measured before treatment and periodically thereafter. Advise patients to avoid excessive alcohol use while taking RECORLEV [see Contraindications (4), Warnings and Precautions (5.1)] .

QT Prolongation

Inform patients that RECORLEV may cause QT prolongation. Advise patients to contact their healthcare provider immediately for signs or symptoms of QT prolongation, which include severe lightheadedness (pre-syncope) or fainting (syncope). Advise patients that an ECG will be taken before treatment and periodically thereafter. Advise patients that potassium and magnesium disturbances may require correction to aid in preventing QT interval prolongation [see Contraindications (4), Warnings and Precautions (5.2)] .

Hypocortisolism

Inform patients that RECORLEV may cause hypocortisolism. Advise patients of the signs and symptoms of hypocortisolism. Advise patients to report signs and symptoms of hypocortisolism to their healthcare provider promptly. Advise patients that cortisol in the blood or urine will be measured before treatment and periodically thereafter [see Warnings and Precautions (5.3)] .

Hypersensitivity Reactions

Inform patients that RECORLEV may cause hypersensitive reactions. Advise patients to contact their healthcare provider if signs or symptoms of hypersensitivity reaction occur [see Contraindications (4), Warnings and Precautions (5.4)] .

Drug Interactions

Inform patients that RECORLEV may interact with many drugs. Advise patients to report to their healthcare provider the use of all prescription and nonprescription medications [see Contraindications (4), Drug Interactions (7)] .

Pregnancy

Advise pregnant patients and females of reproductive potential of the risk to a fetus. Advise females to inform their healthcare provider of a known or suspected pregnancy [see Use in Specific Populations (8.1)] .

Lactation

Advise patients not to breastfeed during treatment with RECORLEV and for one day after the final dose [see Use in Specific Populations (8.2)] .

Infertility

Advise patients of reproductive potential that RECORLEV may impair fertility [see Use in Specific Populations (8.3)] .

Distributed by:

Xeris Pharmaceuticals, Inc.

1375 W Fulton St., Suite 1300

Chicago, IL 60607

1-877-XERIS-37 (1-877-937-4737)

www.xerispharma.com

RECORLEV® is a registered trademark licensed exclusively in the U.S. to Xeris Pharmaceuticals, Inc.

Copyright © 2023 Xeris Pharmaceuticals, Inc. All rights reserved.

MEDICATION GUIDE RECORLEV® (re kor ' lev) (levoketoconazole) tablets, for oral use

What is the most important information I should know about RECORLEV?

RECORLEV can cause serious side effects, including:

- Liver damage (hepatotoxicity).Hepatotoxicity can happen in people who take RECORLEV. Some people who are treated with ketoconazole, a medicine like the active ingredient in RECORLEV, had serious liver problems that required a liver transplant or led to death.

Call your healthcare provider right away if you have any of the following signs or symptoms:

- pain on the upper right side of your stomach area (abdomen) associated with nausea
- unusual fatigue
- yellowing of your skin or the whites of your eyes (jaundice)
- unusual bruising or bleeding

RECORLEV should not be used if you have any of the following conditions:

- cirrhosis
- active or poorly controlled liver disease
- frequent stones in your gallbladder (cholelithiasis)
- history of liver problems due to use of a drug

Your healthcare provider will do liver tests before and during treatment with RECORLEV.

- Heart rhythm problems (QT prolongation).RECORLEV can cause a heart problem called QT interval prolongation, or QT prolongation. QT prolongation can cause irregular heartbeats that can be life threatening.

Call your healthcare provider right away ifyou feel severe lightheadedness or if you faint during treatment with RECORLEV.

- Low blood electrolyte levels of potassium and magnesium can increase your chances of QT prolongation during treatment with RECORLEV.

Your healthcare provider will check your heart with a test called an electrocardiogram (ECG) and do blood tests to check your blood electrolyte levels before and during treatment with RECORLEV.

RECORLEV should not be taken with certain other medicines that cause QT prolongation. Talk to your healthcare provider about the medicines you are taking before you start taking RECORLEV.

- Low cortisol levels (adrenal insufficiency).Adrenal insufficiency is a condition in which the adrenal glands do not make enough steroid hormones, such as cortisol. RECORLEV may cause adrenal function insufficiency by excessively lowering production of cortisol.

Call your healthcare provider right away ifyou have one or more of the following symptoms, as these may be symptoms of reduced adrenal function:

- nausea or vomiting

- dizziness

- unusual fatigue

- low blood pressure (hypotension)

- unexplained stomach pain (abdomen)

- abnormal electrolyte levels

- loss of appetite

- low blood sugar (hypoglycemia)

- body aches

Your healthcare provider will collect blood or urine samples to measure your cortisol.

What is RECORLEV?

- RECORLEV is a prescription medicine used to treat high cortisol (endogenous hypercortisolemia) levels in adult patients with Cushing’s syndrome (CS) who cannot have surgery or who have had surgery that did not cure their Cushing's syndrome.
- It is not known if RECORLEV is safe and effective for the treatment of fungal infections. RECORLEV is not to be used for treatment of fungal infections.

Do not take RECORLEV if you:

- have or have had liver problems.
- take certain other medicines that cause QT prolongation.
- have a history of certain heart problems which may include one the following conditions: torsades de pointes, ventricular tachycardia, ventricular fibrillation, or long QT syndrome.
- are allergic to levoketoconazole, ketoconazole, or any of the ingredients in RECORLEV. See the end of this Medication Guide for a complete list of ingredients in RECORLEV.
- take certain medicines that may affect how your liver works (for example, CYP3A4 inhibitors). If you are not sure if you take these medicines, please ask your healthcare provider.

Before taking RECORLEV, tell your healthcare provider about all of your medical conditions, including if you:

- have or have had liver problems.
- have any heart problems, including a condition called long QT syndrome.
- have a history of low blood levels of potassium or magnesium.
- are pregnant or plan to become pregnant. RECORLEV may harm your unborn baby. Tell your healthcare provider right away if you become pregnant during treatment with RECORLEV or think you might be pregnant.
- are breastfeeding or plan to breastfeed. RECORLEV can pass into your breast milk. You and your healthcare provider should decide if you should take RECORLEV or breastfeed. You should not breastfeed during treatment with RECORLEV and for 1 day after final dose.

Tell your healthcare provider about all the medicines you take,including prescription and over-the-counter medicines, vitamins, and herbal supplements. RECORLEV and other medicines may affect each other causing side effects. RECORLEV may affect the way other medicines work, and other medicines may affect how RECORLEV works.

How should I take RECORLEV?

- Take RECORLEV exactly as your healthcare provider tells you. Your healthcare provider will tell you how much RECORLEV to take and when to take it.
- RECORLEV is taken by mouth 2 times a day, with or without food.
- Your healthcare provider may decrease, temporarily hold, or permanently stop your treatment with RECORLEV if needed.
- If you miss a dose of RECORLEV, take the next dose at your regular scheduled time.
- If you take too much RECORLEV, call your healthcare provider or go to the nearest hospital emergency room right away.

What should I avoid while taking RECORLEV?

- Drinking alcohol to excess while taking RECORLEV may increase your chances of having serious side effects.

What are the possible side effects of RECORLEV?

RECORLEV may cause serious side effects, including:

- See "What is the most important information I should know about RECORLEV?”
- Hypersensitivity reactions.Serious allergic reactions can happen in people who take RECORLEV. Call your healthcare provider right away, or visit an emergency center, if you get a rash, itching, hives, fever, swelling of the lips or tongue, chest pain, or have trouble breathing. These could be signs of a serious allergic reaction.

- Risks related to decreased testosterone.RECORLEV may lower testosterone levels in males and females. Call your healthcare provider if you have any of these symptoms:
- Males: breast enlargement (gynecomastia) and erectile dysfunction (impotence)
- Females: low desire for sex (decreased libido) and mood changes.

The most common side effects of RECORLEV includenausea/vomiting, hypokalemia (low potassium), hemorrhage (easy bleeding)/contusion (easy bruising), high blood pressure, headache, liver injury, abnormal uterine bleeding, erythema (redness of the skin), fatigue, abdominal pain/dyspepsia (upset stomach), arthritis, upper respiratory infection, myalgia (muscle pain), abnormal heart rhythm, back pain, sleep disturbances, and peripheral edema (fluid retention).

RECORLEV may cause fertility problems in females and males, which may affect your ability to have children. Talk to your healthcare provider if you have concerns about fertility.

These are not all the possible side effects of RECORLEV.

Call your healthcare provider for medical advice about side effects. You may report side effects to FDA at 1-800-FDA-1088.

How should I store RECORLEV?

- Store RECORLEV at room temperature between 68°F to 77°F (20°C to 25°C).

Keep RECORLEV and all medicines out of the reach of children.

General information about the safe and effective use of RECORLEV.

Medications are sometimes prescribed for purposes other than those listed in this Medication Guide. Do not use RECORLEV for a condition for which it was not prescribed. Do not give RECORLEV to other people, even if they have the same symptoms that you have. It may harm them. You can ask your pharmacist or healthcare provider for information about RECORLEV that is written for health professionals.

What are the ingredients in RECORLEV?

Active ingredients:levoketoconazole.

Inactive ingredients:colloidal silicon dioxide, lactose monohydrate, magnesium stearate, modified corn starch, and silicified microcrystalline cellulose.

Distributed by: Xeris Pharmaceuticals, Inc., Chicago, IL 60607

For more information, go to www.Recorlev.com or call 1-877-937-4737.

This Medication Guide has been approved by the U.S. Food and Drug Administration Issued: 06/2023

Principal Display Panel-Bottle Label (50 Tablets)

NDC 72065-003-01
50 Tablets Rx only

Recorlev®

(levoketoconazole)

Tablets 150 mg

Dispense the Medication Guide
provided separately to each patient.